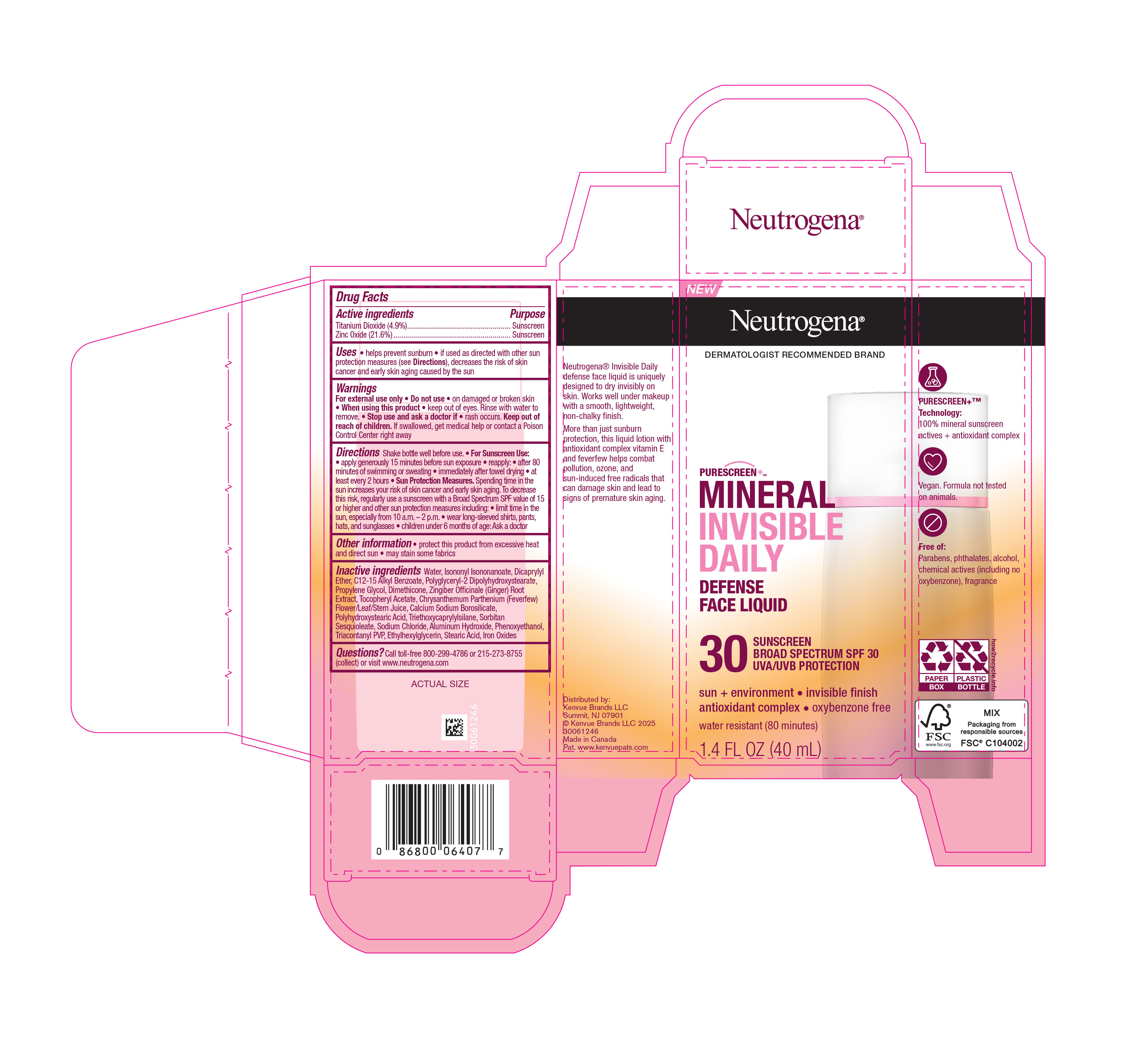 DRUG LABEL: Neutrogena Mineral Invisible Daily Defense Face Sunscreen Broad Spectrum SPF 30
NDC: 69968-0815 | Form: LOTION
Manufacturer: Kenvue Brands LLC
Category: otc | Type: HUMAN OTC DRUG LABEL
Date: 20250728

ACTIVE INGREDIENTS: TITANIUM DIOXIDE 49 mg/1 mL; ZINC OXIDE 216 mg/1 mL
INACTIVE INGREDIENTS: SORBITAN SESQUIOLEATE; ALKYL (C12-15) BENZOATE; POLYGLYCERYL-2 DIPOLYHYDROXYSTEARATE; PROPYLENE GLYCOL; GINGER; .ALPHA.-TOCOPHEROL ACETATE; TRIETHOXYCAPRYLYLSILANE; SODIUM CHLORIDE; ALUMINUM HYDROXIDE; PHENOXYETHANOL; TRIACONTANYL PVP (WP-660); ETHYLHEXYLGLYCERIN; STEARIC ACID; FERROUS OXIDE; FEVERFEW; ISONONYL ISONONANOATE; DICAPRYLYL ETHER; DIMETHICONE; WATER; CALCIUM SODIUM BOROSILICATE

Neutrogena Mineral Invisible Daily Defense Face Sunscreen Broad Spectrum SPF 30

Drug Facts

ACTIVE INGREDIENT

Active ingredients | Purpose
Titanium Dioxide (4.9%) | Sunscreen
Zinc Oxide (21.6%) | Sunscreen

Uses

- helps prevent sunburn
- if used as directed with other sun protection measures (see Directions), decreases the risk of skin cancer and early skin aging caused by the sun

Warnings

For external use only

- Do not use • on damaged or broken skin

When using this product

- keep out of eyes. Rinse with water to remove.

- Stop use and ask a doctor if • rash occurs.

Keep out of reach of children. If swallowed, get medical help or contact a Poison Control Center right away

Directions

Shake bottle well before use.

• For Sunscreen Use:

• apply generously 15 minutes before sun exposure

• reapply:

• after 80 minutes of swimming or sweating

• immediately after towel drying

• at least every 2 hours

• Sun Protection Measures. Spending time in the sun increases your risk of skin cancer and early skin aging. To decrease this risk, regularly use a sunscreen with a Broad Spectrum SPF value of 15 or higher and other sun protection measures including:

• limit time in the sun, especially from 10 a.m. – 2 p.m.

• wear long-sleeved shirts, pants, hats, and sunglasses

• children under 6 months of age: Ask a doctor

Other information

- protect this product from excessive heat and direct sun
- may stain some fabrics

Inactive ingredients

Water, Isononyl Isononanoate, Dicaprylyl Ether, C12-15 Alkyl Benzoate, Polyglyceryl-2 Dipolyhydroxystearate, Propylene Glycol, Dimethicone, Zingiber Officinale (Ginger) Root Extract, Tocopheryl Acetate, Chrysanthemum Parthenium (Feverfew) Flower/Leaf/Stem Juice, Calcium Sodium Borosilicate, Polyhydroxystearic Acid, Triethoxycaprylylsilane, Sorbitan Sesquioleate, Sodium Chloride, Aluminum Hydroxide, Phenoxyethanol, Triacontanyl PVP, Ethylhexylglycerin, Stearic Acid, Iron Oxides

Questions?

Call toll-free 800-299-4786 or 215-273-8755 (collect) or visit www. neutrogena.com

Distributed by:

Kenvue Brands LLC
Summit, NJ 07901

PRINCIPAL DISPLAY PANEL - 40 mL Bottle Label

NEW

Neutrogena®

DERMATOLOGIST RECOMMENDED BRAND

PURESCREEN+TM

MINERAL

INVISIBLE

DAILY

DEFENSE

FACE LIQUID

30

SUNSCREEN

BROAD SPECTRUM SPF 30

UVA/UVB PROTECTION

sun + environment ∙ invisible finish

antioxidant complex ∙ oxybenzone free

water resistant (80 minutes)

1.4 FL OZ (40 mL)